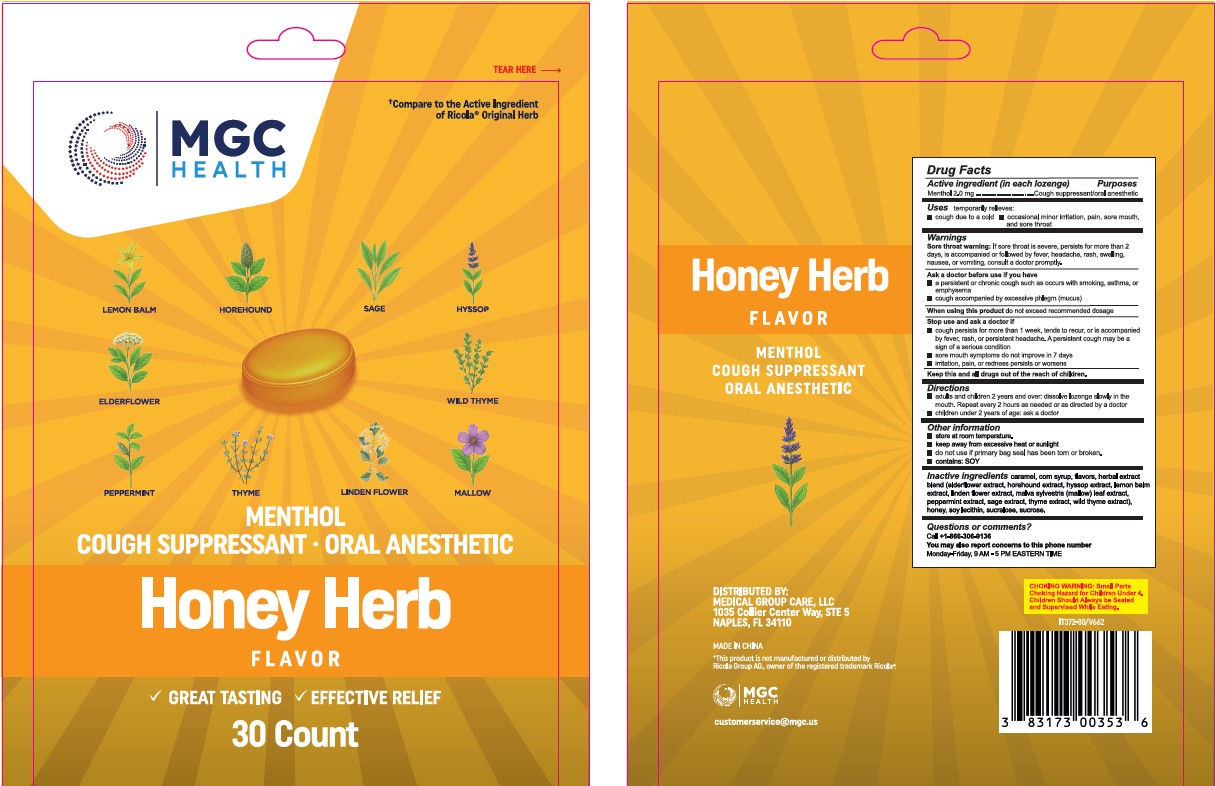 DRUG LABEL: MGC Health Cough Drops
NDC: 83173-143 | Form: LOZENGE
Manufacturer: Medical Group Care LLC
Category: otc | Type: HUMAN OTC DRUG LABEL
Date: 20250925

ACTIVE INGREDIENTS: MENTHOL 2 mg/1 1
INACTIVE INGREDIENTS: CARAMEL; CORN SYRUP; LECITHIN, SOYBEAN; SUCROSE; SUCRALOSE; HONEY; SAMBUCUS NIGRA FLOWER; HOREHOUND; HYSSOPUS OFFICINALIS FLOWERING TOP; LEMON BALM OIL; TILIA CORDATA FLOWER; MALVA SYLVESTRIS LEAF; PEPPERMINT; SAGE; THYME; WILD THYME

Honey Herb Flavor Menthol Cough Drop MGC-Xiamen

Drug Facts

Purpose

Cough suppressant/Oral anesthetic

Active Ingredient (in each drop)

Menthol, 2.0 mg

Uses

temporarily relieves:

- cough due to a cold
- occasional minor irritation and pain due to sore throat or sore mouth

Warnings

Sore throat warning:If sore throat is severe, persists for more than 2 days, is accompanied or followed by fever, headache, rash, swelling, nausea, or vomiting, consult a doctor promptly.

Ask doctor before use if you have

- persistent chronic cough such as occurs with smoking, asthma, or emphysema
- cough accompanied by excessive phlegm (mucus)

When using this productdo not exceed recommended dosage

Stop use and ask a doctor if

- cough persists for more than 1 week, tends to recur, or is accompanied by fever, rash, or persistent headache. These could be signs of a serious condition.
- sore mouth does not improve in 7 days
- irritation, pain, or redness persists or worsens

Directions

- adults and children 2 years and over: dissolve lozenge slowly in the
  mouth. Repeat every 2 hours as needed or as directed by a doctor
- children under 2 years of age: ask a doctor

Other Information

- store at room temperature.
- keep away from excessive heat or sunlight
- do not use if primary bag seal has been torn or broken.
- contains: SOY

Inactive Ingredients

caramel, corn syrup, flavors, herbal extract
blend (elderflower extract, horehound extract, hyssop extract, lemon
balm extract, linden flower extract, malva sylvestris (mallow) leaf extract,
peppermint extract, sage extract, thyme extract, wild thyme extract), honey,
soy lecithin, sucralose, sucrose.

Questions or comments?

Call +1-866-306-9136
You may also report concerns to this phone number
Monday-Friday, 9 AM - 5 PM EASTERN TIME